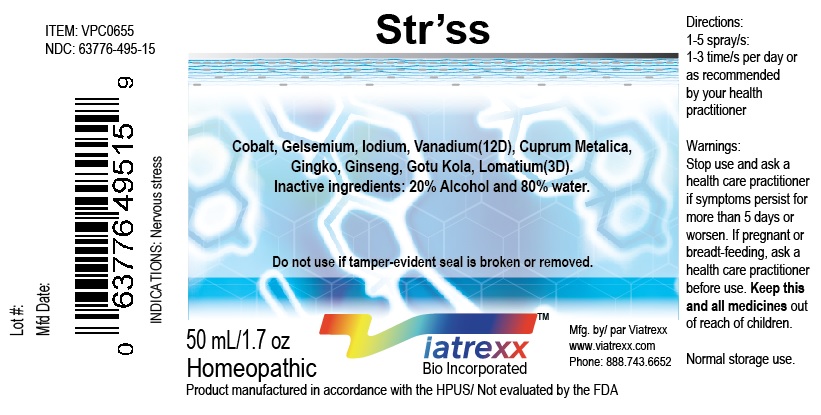 DRUG LABEL: Viatrexx-Str ss
NDC: 63776-495 | Form: SPRAY
Manufacturer: VIATREXX BIO INCORPORATED
Category: homeopathic | Type: HUMAN OTC DRUG LABEL
Date: 20190319

ACTIVE INGREDIENTS: Cobalt 12 [hp_X]/1 mL; Copper 3 [hp_X]/1 mL; Gelsemium Sempervirens Root 12 [hp_X]/1 mL; Ginkgo 3 [hp_X]/1 mL; American Ginseng 3 [hp_X]/1 mL; Centella Asiatica Leaf 3 [hp_X]/1 mL; Iodine 12 [hp_X]/1 mL; Lomatium Dissectum Whole 3 [hp_X]/1 mL; Vanadium 12 [hp_X]/1 mL
INACTIVE INGREDIENTS: Water; Alcohol

Str'ss

Active Ingredients

Cobalt 12X, Copper met 3X, Gelsemium 12X, Ginko 3X, Ginseng 3X, Gotu kola 3X, Iodium 12X, Lomatium 3X, Vanadium 12X

Purpose

Cobalt
Cuprum met
Gelsemium
Ginko
Ginseng
Gotu kola
Iodium
Lomatium
Vanadium

Adaptogenic
Anti-spasmodic
Drainage, energy
Circulation support
adaptogenic
Support
Energy support
Drainage
Nutritional support

Description

Viatrexx-Str ss is a homeopathic product composed of physiological (low dose and low low dose) natural micro nutrients. These micro particles are designed to nourish the system.

Uses

To support in times of stress.

Warnings

Stop use and ask a health care practitioner if symptoms persist for more than five days or worsen. If pregnant or breastfeeding, ask a health care practitioner before use.

Dosage

1-3 spray(s); 1-3 time(s) per day or as recommended by your health care practitioner.

Inactive Ingredients

20% Alcohol and 80% Water

Other Information

Product availability

Product may be acquired in 0.5, 30, 50, 100, 250 mL bottles.

References upon request

To report SUSPECTED ADVERSE REACTIONS, contact the FDA at 1-800-FDA-1088 or www.fda.gov/medwatch

Distributed by
Viatrexx Bio Incorporated
Newark, DE, USA, 19713

Manufactured by
8046255 Canada Inc
Beloeil, Qc, J3G 6S3
Date of last revision March 2019

For Questions and comments
Info@Viatrexx.com
www.Viatrexx.com

PACKAGE LABEL.PRINCIPAL DISPLAY PANEL

NDC: 63776-495-11
Item: VPC0655
Viatrexx Bio Incorporated
Viatrexx- Str ss
Box of 1 X 0.5 mL ampule
For Oral and Topical Use
Expiry date: Lot #:
Manufactured for:
Viatrexx Bio Incorporated Newark, DE, USA, 19713
www.Viatrexx.com
Ingredients, homeopathic
See insert or www.viatrexx.com
Inactives: Alcohol 20%, Water 80%

NDC: 63776-495-14
Item: VPC0655
Viatrexx Bio Incorporated
Viatrexx-Str ss
Box of 1 X 30 mL spray bottle
For Oral and Topical Use
Expiry date: Lot #:
Manufactured for:
Viatrexx Bio Incorporated Newark, DE, USA, 19713
www.Viatrexx.com
Ingredients, homeopathic
See insert or www.viatrexx.com
Inactives: Alcohol 20%, Water 80%

NDC: 63776-495-15
Item: VPC0655
Viatrexx Bio Incorporated
Viatrexx-Str ss
Box of 1 X 50 mL spray bottle
For Oral and Topical Use
Expiry date: Lot #:
Manufactured for:
Viatrexx Bio Incorporated Newark, DE, USA, 19713
www.Viatrexx.com
Ingredients, homeopathic
See insert or www.viatrexx.com
Inactives: Alcohol 20%, Water 80%

NDC: 63776-495-16
Item: VPC0655
Viatrexx Bio Incorporated
Viatrexx-Str ss
Box of 1 X 100 mL bottle
For Oral and Topical Use
Expiry date: Lot #:
Manufactured for:
Viatrexx Bio Incorporated Newark, DE, USA, 19713
www.Viatrexx.com
Ingredients, homeopathic
See insert or www.viatrexx.com
Inactives: Alcohol 20%, Water 80%

NDC: 63776-495-17
Item: VPC0655
Viatrexx Bio Incorporated
Viatrexx-Str ss
Box of 1 X 250 mL bottle
For Oral and Topical Use
Expiry date: Lot #:
Manufactured for:
Viatrexx Bio Incorporated Newark, DE, USA, 19713
www.Viatrexx.com
Ingredients, homeopathic
See insert or www.viatrexx.com
Inactives: Alcohol 20%, Water 80%